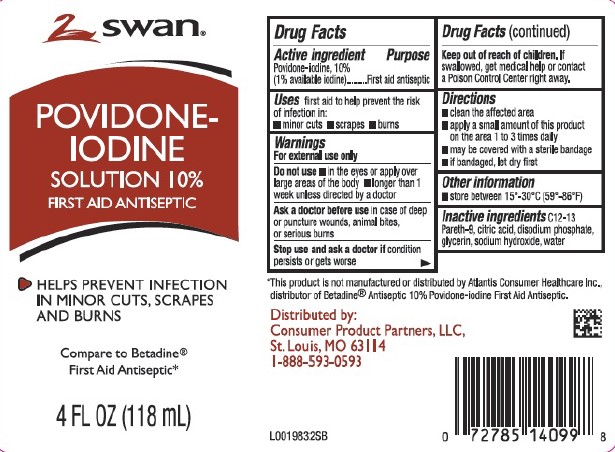 DRUG LABEL: Povidone Iodine Solution First Aid Antiseptic
NDC: 11344-050 | Form: SOLUTION
Manufacturer: Consumer Product Partners, LLC
Category: otc | Type: HUMAN OTC DRUG LABEL
Date: 20250227

ACTIVE INGREDIENTS: POVIDONE-IODINE 10 mg/1 mL
INACTIVE INGREDIENTS: C12-13 PARETH-9; CITRIC ACID MONOHYDRATE; SODIUM PHOSPHATE, DIBASIC, ANHYDROUS; GLYCERIN; SODIUM HYDROXIDE; WATER

Swan 050.002/050AE
Povidone-Iodine Solution, 10%

Active ingredient

Povidone-iodine, 10%

(1% available iodine)

Purpose

First aid antiseptic

Uses

first aid to help prevent the risk of infection in:

- minor cuts
- scrapes
- burns

Warnings

For external use only

Do not use

- in the eyes or apply over large areas of the body
- longer than 1 week unless directed by a doctor

Ask a doctor before use

in case of deep or puncture wounds, animal bites, or serious burns

Stop use and ask a doctor if

condition persists or gets worse

Keep out of reach of children.

If swallowed, get medical help or contact a Poison Control Center right away.

Directions

- clean the affected area
- apply a small amount of this product on the area 1 to 3 times daily
- may be covered with a sterile bandage
- if bandaged, let dry first.

Other information

store between 15° - 30°C (59°-86°F)

Inactive ingredients

C12-13 Pareth-9, citric acid, disodium phosphate, glycerin, sodium hydroxide, water

Disclaimer

*This product is not manufactured or distributed by Atlantis Consumer Healthcare Inc., distributor of Betadine®Antiseptic 10% Povidone-iodine First Aid Antiseptic.

Adverse reaction

Distributed by:

Consumer Product Partners, LLC

St. Louis, MO 63114

1-888-593-0593

Principal display panel

Swan ®

POVIDONE-IODINE SOLUTION 10%

FIRST AID ANTISEPTIC

- HELPS PREVENT INFECTION IN MINOR CUTS, SCRAPES, AND BURNS

Compare to Betadine®First Aid Antiseptic*

4 FL OZ (118 mL)